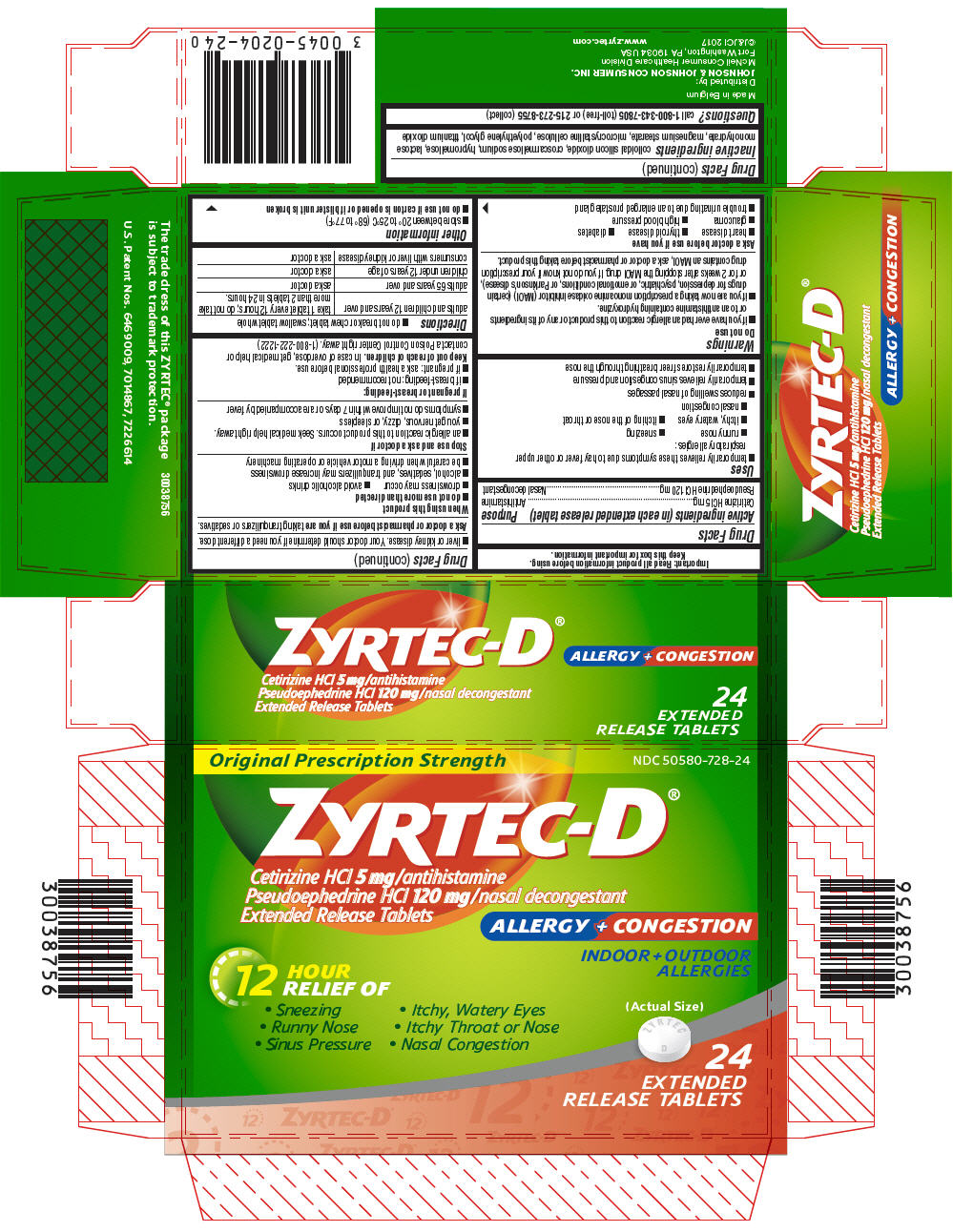 DRUG LABEL: ZYRTEC-D
NDC: 50580-728 | Form: TABLET, FILM COATED, EXTENDED RELEASE
Manufacturer: Kenvue Brands LLC
Category: otc | Type: HUMAN OTC DRUG LABEL
Date: 20250612

ACTIVE INGREDIENTS: CETIRIZINE HYDROCHLORIDE 5 mg/1 1; PSEUDOEPHEDRINE HYDROCHLORIDE 120 mg/1 1
INACTIVE INGREDIENTS: SILICON DIOXIDE; CROSCARMELLOSE SODIUM; HYPROMELLOSE, UNSPECIFIED; LACTOSE MONOHYDRATE; MAGNESIUM STEARATE; MICROCRYSTALLINE CELLULOSE; POLYETHYLENE GLYCOL, UNSPECIFIED; TITANIUM DIOXIDE

ZYRTEC-D
Allergy Plus Congestion

Drug Facts

ACTIVE INGREDIENT

Active ingredients (in each extended release tablet) | Purpose
Cetirizine HCl 5 mg | Antihistamine
Pseudoephedrine HCl 120 mg | Nasal decongestant

Uses

- temporarily relieves these symptoms due to hay fever or other upper respiratory allergies:
  - runny nose
  - sneezing
  - itchy, watery eyes
  - itching of the nose or throat
  - nasal congestion
- reduces swelling of nasal passages
- temporarily relieves sinus congestion and pressure
- temporarily restores freer breathing through the nose

Warnings

Do not use

- if you have ever had an allergic reaction to this product or any of its ingredients or to an antihistamine containing hydroxyzine.
- if you are now taking a prescription monoamine oxidase inhibitor (MAOI) (certain drugs for depression, psychiatric, or emotional conditions, or Parkinson's disease), or for 2 weeks after stopping the MAOI drug. If you do not know if your prescription drug contains an MAOI, ask a doctor or pharmacist before taking this product.

Ask a doctor before use if you have

- heart disease
- thyroid disease
- diabetes
- glaucoma
- high blood pressure
- trouble urinating due to an enlarged prostate gland
- liver or kidney disease. Your doctor should determine if you need a different dose.

Ask a doctor or pharmacist before use if you are taking tranquilizers or sedatives.

When using this product

- do not use more than directed
- drowsiness may occur
- avoid alcoholic drinks
- alcohol, sedatives, and tranquilizers may increase drowsiness
- be careful when driving a motor vehicle or operating machinery

Stop use and ask a doctor if

- an allergic reaction to this product occurs. Seek medical help right away.
- you get nervous, dizzy, or sleepless
- symptoms do not improve within 7 days or are accompanied by fever

If pregnant or breast-feeding:

- if breast-feeding: not recommended
- if pregnant: ask a health professional before use.

Keep out of reach of children. In case of overdose, get medical help or contact a Poison Control Center right away. (1-800-222-1222)

Directions

- do not break or chew tablet; swallow tablet whole

adults and children 12 years and over | take 1 tablet every 12 hours; do not take more than 2 tablets in 24 hours.
adults 65 years and over | ask a doctor
children under 12 years of age | ask a doctor
consumers with liver or kidney disease | ask a doctor

Other information

- store between 20° to 25°C (68° to 77°F)
- do not use if carton is opened or if blister unit is broken

Inactive ingredients

colloidal silicon dioxide, croscarmellose sodium, hypromellose, lactose monohydrate, magnesium stearate, microcrystalline cellulose, polyethylene glycol, titanium dioxide

Questions?

call 1-800-343-7805 (toll-free) or 215-273-8755 (collect)

PRINCIPAL DISPLAY PANEL

Original Prescription Strength
NDC 50580-728-24

ZYRTEC-D®

Cetirizine HCl 5 mg/antihistamine
Pseudoephedrine HCl 120 mg/nasal decongestant
Extended Release Tablets

ALLERGY + CONGESTION

INDOOR + OUTDOOR
ALLERGIES

12
HOUR
RELIEF OF

- Sneezing
- Itchy, Watery Eyes
- Runny Nose
- Itchy Throat or Nose
- Sinus Pressure
- Nasal Congestion

(Actual Size)

24
EXTENDED
RELEASE TABLETS